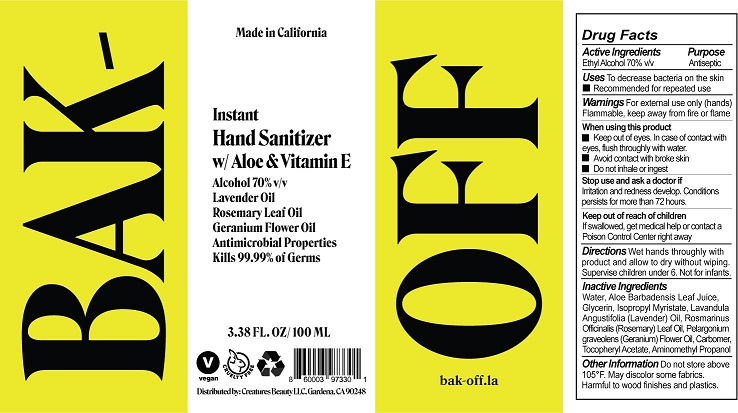 DRUG LABEL: BAK-OFF HAND SANITIZER

NDC: 50518-305 | Form: GEL
Manufacturer: CUSTOM RESEARCH LABS INC
Category: otc | Type: HUMAN OTC DRUG LABEL
Date: 20220329

ACTIVE INGREDIENTS: ALCOHOL 70 mL/100 mL
INACTIVE INGREDIENTS: WATER; ALOE VERA LEAF; GLYCERIN; ISOPROPYL MYRISTATE; LAVENDER OIL; ROSEMARY OIL; GERANIUM OIL, ALGERIAN TYPE; CARBOMER HOMOPOLYMER, UNSPECIFIED TYPE; .ALPHA.-TOCOPHEROL ACETATE; AMINOMETHYLPROPANOL

CRL (as CMO) - BAK-OFF HAND SANITIZER - 70% ETHYL ALCOHOL (50518-305)

ACTIVE INGREDIENT

ETHYL ALCOHOL 70%

PURPOSE

ANTISEPTIC

USES

TO DECREASE BACTERIA ON THE SKIN

RECOMMENDED FOR REPEATED USE

WARNINGS

FOR EXTERNAL USE ONLY (HANDS).

FLAMMABLE, KEEP AWAY FROM FIRE OR FLAME.

WHEN USING THIS PRODUCT

- KEEP OUT OF EYES. IN CASE OF CONTACT WITH EYES, FLUSH THOROUGHLY WITH WATER.
- AVOID CONTACT WITH BROKEN SKIN
- DO NOT INHALE OR INHEST

STOP USE AND ASK A DOCTOR IF

- IRRITATION AND REDNESS DEVELOP
- CONDITION PERSISTS FOR MORE THAN 72 HOURS

KEEP OUT OF REACH OF CHILDREN.

IF SWALLOWED, GET MEDICAL HELP OR CONTACT A POISON CONTROL CENTER RIGHT AWAY.

DIRECTIONS

WET HANDS THOROUGHLY WITH PRODUCT AND ALLOW TO DRY WITHOUT WIPING

- FOR CHILDREN UNDER 6, USE ONLY UNDER ADULT SUPERVISION
- NOT RECOMMENDED FOR INFANTS

OTHER INFORMATION

DO NOT STORE ABOVE 105°F

- MAY DISCOLOR SOME FABRICS
- HARMFUL TO WOOD FINISHES AND PLASTICS

INACTIVE INGREDIENTS

WATER, ALOE BARBADENSIS LEAF JUICE, GLYCERIN, ISOPROPYL MYRISTATE, LAVANDULA ANGUSTIFOLIA (LAVENDER) OIL, ROSMARINUS OFFICINALIS (ROSEMARY) LEAF OIL, PELARGONIUM GRAVEOLENS (GERANIUM) FLOWER OIL, CARBOMER, TOCOPHERYL ACETATE, AMINOMETHYL PROPANOL